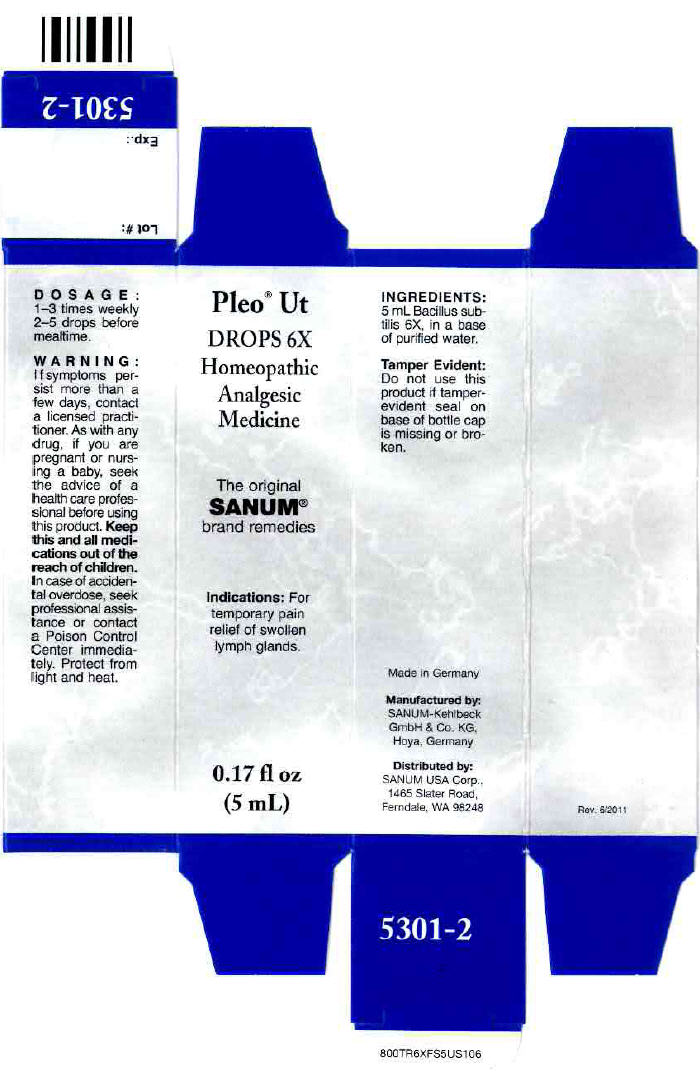 DRUG LABEL: Pleo Ut
NDC: 60681-5301 | Form: SOLUTION/ DROPS
Manufacturer: Sanum Kehlbeck GmbH & Co. KG
Category: homeopathic | Type: HUMAN OTC DRUG LABEL
Date: 20120309

ACTIVE INGREDIENTS: bacillus subtilis 6 [hp_X]/5 mL
INACTIVE INGREDIENTS: water

Pleo® Ut
DROPS 6X

PURPOSE

INDICATIONS AND USAGE

Homeopathic Analgesic Medicine

0.17 fl oz
(5 mL)

DOSAGE

1–3 times weekly 2–5 drops before mealtime.

WARNING

If symptoms persist more than a few days, contact a licensed practitioner. As with any drug, if you are pregnant or nursing a baby, seek the advice of a health care professional before using this product.

KEEP OUT OF REACH OF CHILDREN

Keep this and all medications out of the reach of children. In case of accidental overdose, seek professional assistance or contact a Poison Control Center immediately.

STORAGE AND HANDLING

Protect from light and heat.

ACTIVE INGREDIENT

INGREDIENTS

5 mL Bacillus subtilis 6X, in a base of purified water.

Tamper Evident

Do not use this product if tamper-evident seal on base of bottle cap is missing or broken.

Manufactured by:
SANUM-Kehlbeck
GmbH & Co. KG,
Hoya, Germany

Distributed by:
SANUM USA Corp.,
1465 Slater Road,
Ferndale, WA 98248

PRINCIPAL DISPLAY PANEL - 5 mL Bottle Carton

Pleo® Ut

DROPS 6X
Homeopathic
Analgesic
Medicine

The original
SANUM®
brand remedies

Indications: For
temporary pain
relief of swollen
lymph glands.

0.17 fl oz
(5 mL)